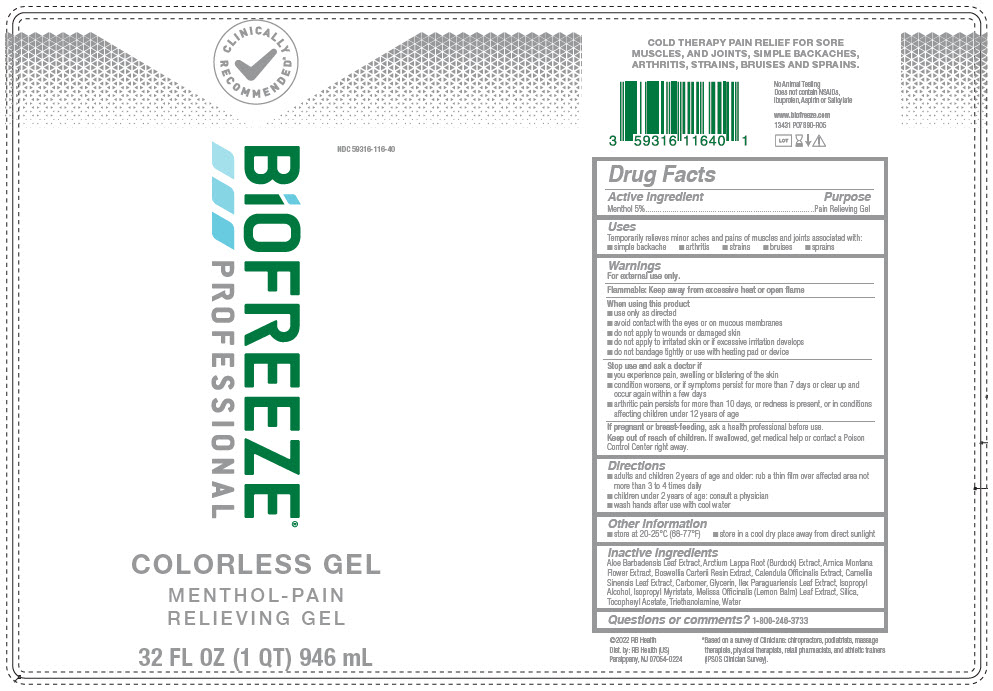 DRUG LABEL: Biofreeze Professional Colorless
NDC: 59316-116 | Form: GEL
Manufacturer: RB Health (US) LLC
Category: otc | Type: HUMAN OTC DRUG LABEL
Date: 20241227

ACTIVE INGREDIENTS: MENTHOL, UNSPECIFIED FORM 50 mg/1 mL
INACTIVE INGREDIENTS: ALOE VERA LEAF; ARCTIUM LAPPA ROOT; ARNICA MONTANA FLOWER; FRANKINCENSE; CALENDULA OFFICINALIS FLOWER; GREEN TEA LEAF; CARBOMER HOMOPOLYMER, UNSPECIFIED TYPE; GLYCERIN; ILEX PARAGUARIENSIS LEAF; ISOPROPYL ALCOHOL; ISOPROPYL MYRISTATE; MELISSA OFFICINALIS LEAF; SILICON DIOXIDE; .ALPHA.-TOCOPHEROL ACETATE; TROLAMINE; WATER

Biofreeze Professional Colorless Gel

Active Ingredients:

Menthol USP 5%

Purpose

Pain Relieving Gel

Uses:

Temporarily relieves from minor aches and pains of muscles and joints associated with: • simple backache • arthritis • strains • bruises • sprains

Warnings:

For external use only

Flammable: Keep away from excessive heat or open flame

When using this product:

• Use only as directed • Avoid contact with the eyes or on mucous membranes • Do not apply to wounds or damaged skin • Do not apply to irritated skin or if excessive irritation develops • Do not bandage tightly or use with
heating pad or device

Stop use and ask a doctor If:

You experience pain, swelling or blistering of the skin; condition worsens, or if symptoms persist for more than 7 days, or clear up and occur again within a few days; arthritic pain persists for more than 10 days, or redness is present, or in conditions affecting children under 12 years of age

If pregnant or breast-feeding:

Ask a health professional before use

Keep out of reach of children:

If swallowed, get medical help or contact a Poison Control Center right away.

Directions:

• Adults and Children 2 years of age and older: Rub a thin film over affected areas not more than 3 to 4 times daily;
•Children under 2 years of age: Consult a physician
• wash hands after use with cool water

Other information:

store at 20-25° C (68-77°F) - store in a cool dry place away from direct sunlight

Inactive Ingredients:

Aloe Barbadensis Leaf Extract, Arctium Lappa Root (Burdock) Extract, Arnica Montana Flower Extract, Boswellia Carterii Resin Extract, Calendula Officinalis Extract, Camellia Sinensis Leaf Extract, Carbomer, Glycerin, Ilex Paraguariensis Leaf Extract, Isopropyl Alcohol, Isopropyl Myristate, Melissa Officinalis (Lemon Balm) Leaf Extract, Silica, Tocopheryl Acetate, Triethanolamine, Water.

Questions or Comments:

1-800-246-3733

PRINCIPAL DISPLAY PANEL - 946 mL Bottle Label

CLINICALLY
RECOMMENDED*

BiOFREEZE®
PROFESSIONAL

NDC 59316-116-40

COLORLESS GEL

MENTHOL-PAIN
RELIEVING GEL

32 FL OZ (1 QT) 946 mL